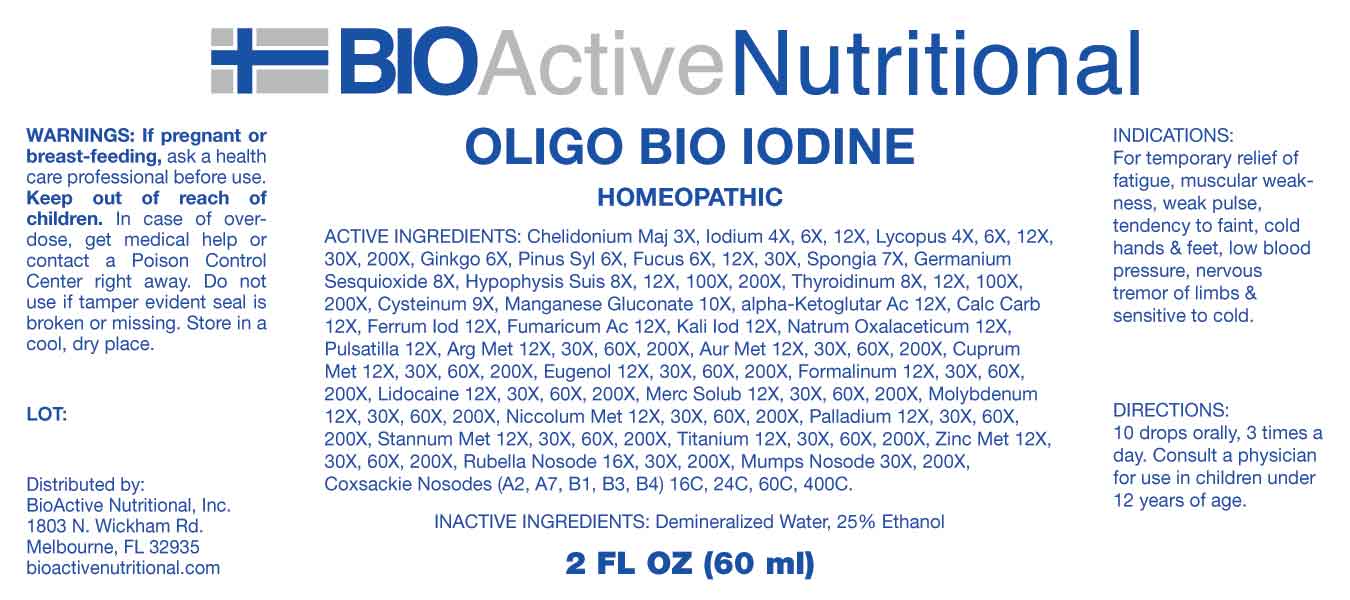 DRUG LABEL: Oligo Bio Iodine
NDC: 43857-0603 | Form: LIQUID
Manufacturer: BioActive Nutritional, Inc.
Category: homeopathic | Type: HUMAN OTC DRUG LABEL
Date: 20231201

ACTIVE INGREDIENTS: CHELIDONIUM MAJUS WHOLE 3 [hp_X]/1 mL; IODINE 4 [hp_X]/1 mL; LYCOPUS VIRGINICUS WHOLE 4 [hp_X]/1 mL; GINKGO 6 [hp_X]/1 mL; PINUS SYLVESTRIS LEAFY TWIG 6 [hp_X]/1 mL; FUCUS VESICULOSUS 6 [hp_X]/1 mL; SPONGIA OFFICINALIS SKELETON, ROASTED 7 [hp_X]/1 mL; GERMANIUM SESQUIOXIDE 8 [hp_X]/1 mL; SUS SCROFA PITUITARY GLAND 8 [hp_X]/1 mL; SUS SCROFA THYROID 8 [hp_X]/1 mL; CYSTEINE 9 [hp_X]/1 mL; MANGANESE GLUCONATE 10 [hp_X]/1 mL; OXOGLURIC ACID 12 [hp_X]/1 mL; OYSTER SHELL CALCIUM CARBONATE, CRUDE 12 [hp_X]/1 mL; FERROUS IODIDE 12 [hp_X]/1 mL; FUMARIC ACID 12 [hp_X]/1 mL; POTASSIUM IODIDE 12 [hp_X]/1 mL; SODIUM DIETHYL OXALACETATE 12 [hp_X]/1 mL; PULSATILLA VULGARIS WHOLE 12 [hp_X]/1 mL; SILVER 12 [hp_X]/1 mL; GOLD 12 [hp_X]/1 mL; COPPER 12 [hp_X]/1 mL; EUGENOL 12 [hp_X]/1 mL; FORMALDEHYDE 12 [hp_X]/1 mL; LIDOCAINE 12 [hp_X]/1 mL; MERCURIUS SOLUBILIS 12 [hp_X]/1 mL; MOLYBDENUM 12 [hp_X]/1 mL; NICKEL 12 [hp_X]/1 mL; PALLADIUM 12 [hp_X]/1 mL; TIN 12 [hp_X]/1 mL; TITANIUM 12 [hp_X]/1 mL; ZINC 12 [hp_X]/1 mL; RUBELLA VIRUS 16 [hp_X]/1 mL; MUMPS VIRUS 30 [hp_X]/1 mL; HUMAN COXSACKIEVIRUS A2 16 [hp_C]/1 mL; HUMAN COXSACKIEVIRUS A7 16 [hp_C]/1 mL; HUMAN COXSACKIEVIRUS B1 16 [hp_C]/1 mL; HUMAN COXSACKIEVIRUS B3 16 [hp_C]/1 mL; HUMAN COXSACKIEVIRUS B4 16 [hp_C]/1 mL
INACTIVE INGREDIENTS: WATER; ALCOHOL

DRUG FACTS:

ACTIVE INGREDIENTS:

Chelidonium Majus 3X, Iodium 4X, 6X, 12X, Lycopus Virginicus 4X, 6X, 12X, 30X, 200X, Ginkgo Biloba 6X, Pinus Sylvestris 6X, Fucus Vesiculosus 6X, 12X, 30X, Spongia Tosta 7X, Germanium Sesquioxide 8X, Hypophysis Suis 8X, 12X, 100X, 200X, Thyroidinum 8X, 12X, 100X, 200X, Cysteinum 9X, Manganese Gluconate 10X, Alpha-Ketoglutaricum Acidum 12X, Calcarea Carbonica 12X, Ferrum Iodatum 12X, Fumaricum Acidum 12X, Kali Iodatum 12X, Natrum Oxalaceticum 12X, Pulsatilla 12X, Argentum Metallicum 12X, 30X, 60X, 200X, Aurum Metallicum 12X, 30X, 60X, 200X, Cuprum Metallicum 12X, 30X, 60X, 200X, Eugenol 12X, 30X, 60X, 200X, Formalinum 12X, 30X, 60X, 200X, Lidocaine 12X, 30X, 60X, 200X, Mercurius Solubilis 12X, 30X, 60X, 200X, Molybdenum Metallicum 12X, 30X, 60X, 200X, Niccolum Metallicum 12X, 30X, 60X, 200X, Palladium Metallicum 12X, 30X, 60X, 200X, Stannum Metallicum 12X, 30X, 60X, 200X, Titanium Metallicum 12X, 30X, 60X, 200X, Zincum Metallicum 12X, 30X, 60X, 200X, Rubella Nosode 16X,30X, 200X, Parotidinum 30X, 200X, Coxsackie A2 16C, 24C, 60C, 400C, Coxsackie A7 16C, 24C, 60C, 400C, Coxsackie B1 16C, 24C, 60C, 400C, Coxsackie B3 16C, 24C, 60C, 400C, Coxsackie B4 16C, 24C, 60C, 400C.

INDICATIONS:

For temporary relief of fatigue, muscular weakness, weak pulse, tendency to faint, cold hands & feet, low blood pressure, nervous tremor of limbs & sensitive to cold.

WARNINGS:

If pregnant or breast-feeding, ask a health care professional before use.

Keep out of reach of children. In case of overdose, get medical help or contact a Poison Control Center right away.

Do not use if tamper evident seal is broken or missing.

Store in a cool, dry place.

KEEP OUT OF REACH OF CHILDREN:

In case of overdose, get medical help or contact a Poison Control Center right away.

DIRECTIONS:

10 drops orally, 3 times a day. Consult a physician for use in children under 12 years of age.

INDICATIONS:

For temporary relief of fatigue, muscular weakness, weak pulse, tendency to faint, cold hands & feet, low blood pressure, nervous tremor of limbs & sensitive to cold.

INACTIVE INGREDIENTS:

Demineralized Water, 25% Ethanol

QUESTIONS:

Distributed by:

BioActive Nutritional, Inc.

1803 N. Wickham Rd.

Melbourne, FL 32935

bioactivenutritional.com

PACKAGE LABEL DISPLAY:

BIOActive Nutritional

OLIGO BIO IODINE

HOMEOPATHIC

2 FL OZ (60 ml)